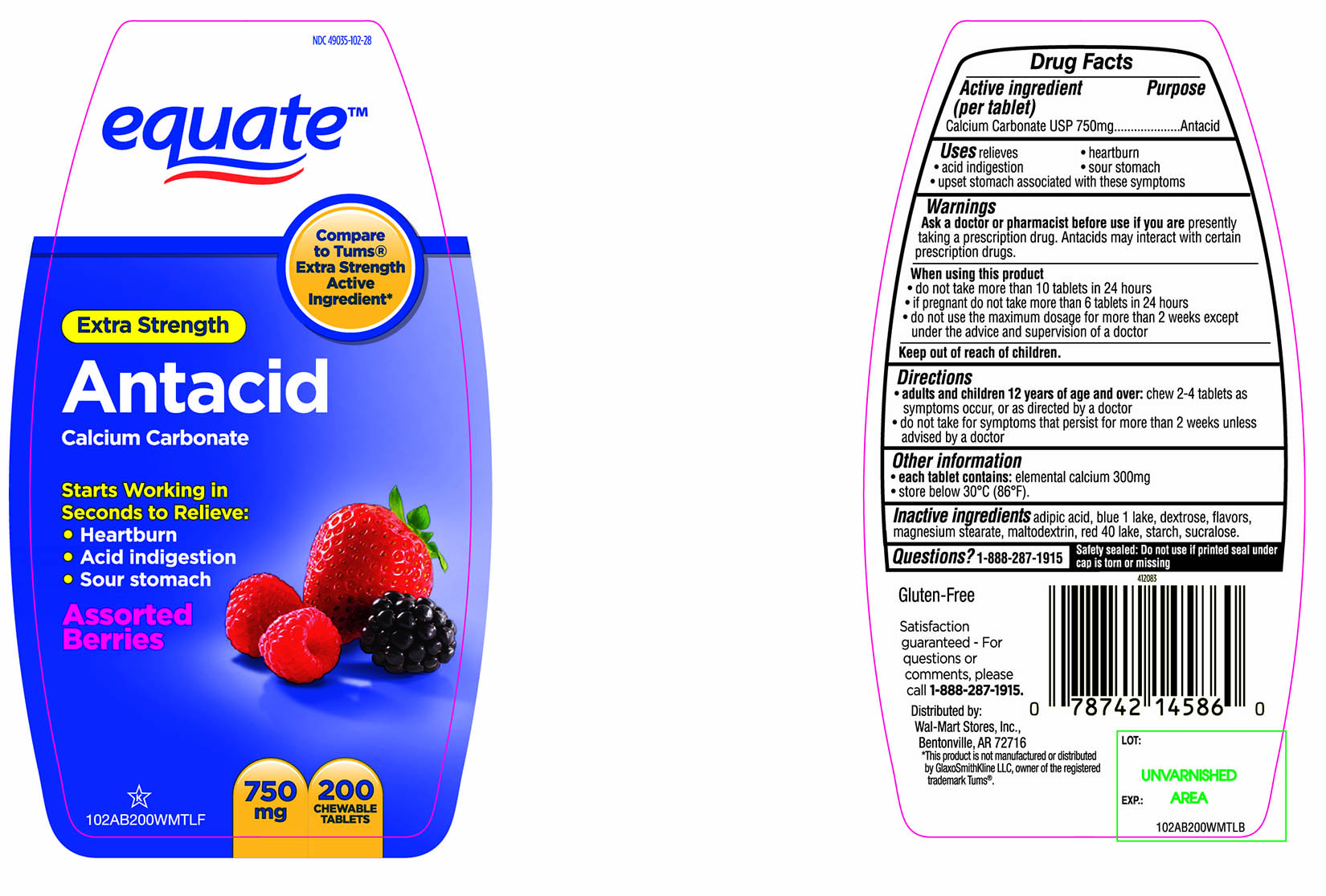 DRUG LABEL: equate Extra Strength Antacid Calcium Carbonate
NDC: 49035-102 | Form: TABLET, CHEWABLE
Manufacturer: Wal-Mart Stores,Inc.,
Category: otc | Type: HUMAN OTC DRUG LABEL
Date: 20160321

ACTIVE INGREDIENTS: CALCIUM CARBONATE 750 mg/1 1
INACTIVE INGREDIENTS: ADIPIC ACID; FD&C BLUE NO. 1; DEXTROSE; MAGNESIUM STEARATE; MALTODEXTRIN; FD&C RED NO. 40; STARCH, CORN; SUCRALOSE

equate Extra Strength Antacid Calcium Carbonate Chewable Tablets

Active ingredient (per tablet)

Calcium Carbonate USP 750mg

Purpose

Antacid

Uses

relieves

• heartburn

• acid indigestion

• sour stomach

• upset stomach associated with these symptoms

Warnings

Ask a doctor or pharmacist before use if you are presentlytaking a prescription drug. Antacids may interact with certain prescription drugs.

When using this product

- do not take more than 10 tablets in 24 hours
- If pregnant do not take more than 6 tablets in 24 hours
- do not use the maximum dosage for more than 2 weeks except under the advice and supervision of a doctor

Directions

- adults and children 12 years of age and over: chew 2-4 tablets as symptoms occur ,or as directed by a doctor
- do not take for symptoms that persist for more than 2 weeks unless advised by a doctor

Other information

• each tablet contains: elemental calcium 300mg

• store below 30°C (86°F).

Inactive ingredients

adipic acid, blue 1 lake, dextrose, flavors, magnesium stearate, maltodextrin, red 40 lake, starch, sucralose,

Questions?

1-888-287-1915

Safety sealed: Do not use if printed seal under cap is torn or missing

Package/Label Principal Display Panel

NDC 49035-102-28

Compare to Tums® Extra Strength Active Ingredient*

Extra Strength

Antacid

Calcium Carbonate

Starts Working in Seconds to Relieve:

- Heartburn
- Acid indigestion
- Sour stomach

Assorted Berries

750 mg

200 CHEWABLE TABLETS

Gluten-Free

Satisfaction guaranteed-

For questions or comments, please call

1-888-287-1915.

Distributed by: Wal-Mart Stores, Inc.,

Bentonville,AR 72716

*This product is not manufactured or distributed by GlaxoSmithKline LLC, owner of the registered trademark, Tums®.